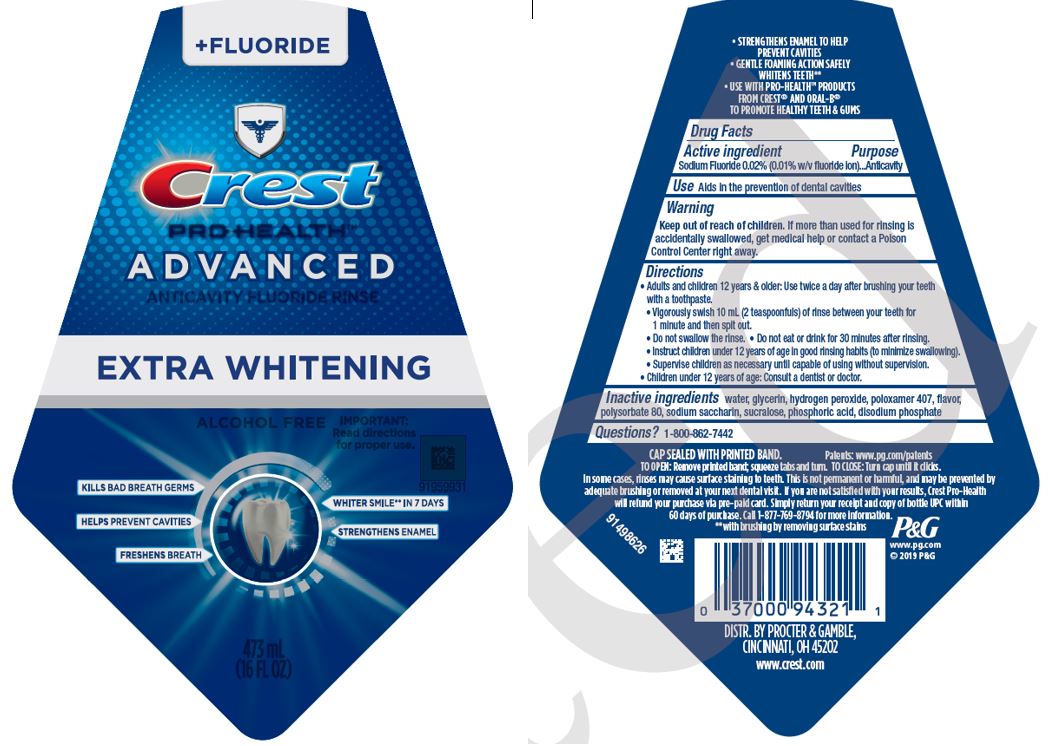 DRUG LABEL: Crest Pro-Health
NDC: 37000-867 | Form: RINSE
Manufacturer: The Procter & Gamble Manufacturing Company
Category: otc | Type: HUMAN OTC DRUG LABEL
Date: 20250307

ACTIVE INGREDIENTS: SODIUM FLUORIDE 0.1 mg/1 mL
INACTIVE INGREDIENTS: WATER; GLYCERIN; HYDROGEN PEROXIDE; POLOXAMER 407; POLYSORBATE 80; SACCHARIN SODIUM; SUCRALOSE; PHOSPHORIC ACID; SODIUM PHOSPHATE, DIBASIC, ANHYDROUS

Crest®
Pro-Health™
Advanced
Extra Whitening

Drug Facts

Active ingredient

Sodium Fluoride 0.02% (0.01% w/v fluoride ion)

Purpose

Anticavity

Use

Aids in the prevention of dental cavities

Warnings

Keep out of reach of children. If more than used for rinsing is accidentally swallowed, get medical help or contact a Poison Control Center right away.

Directions

- Adults and children 12 years & older:
  - Use twice a day after brushing your teeth with a toothpaste.
  - Vigorously swish 10 mL (2 teaspoonfuls) of rinse between your teeth for 1 minute and then spit out.
  - Do not swallow the rinse.
  - Do not eat or drink for 30 minutes after rinsing.
  - Instruct children under 12 years of age in good rinsing habits (to minimize swallowing).
  - Supervise children as necessary until capable of using without supervision.
- Children under 12 years of age: consult a dentist or doctor.

Inactive ingredients

water, glycerin, hydrogen peroxide, poloxamer 407, flavor, polysorbate 80, sodium saccharin, sucralose, phosphoric acid, disodium phosphate

Questions?

1-800-285-9139

DISTR. BY PROCTER & GAMBLE,
CINCINNATI, OH 45202

PRINCIPAL DISPLAY PANEL - 473 mL Bottle Label

+FLUORIDE

CREST

PRO-HEALTH

ADVANCED

ANTICAVITY FLUORIDE RINSE

EXTRA WHITENING

ALCOHOL FREE

IMPORTANT:

Read directions

for proper use.

KILLS BAD BREATH GERMS

WHITER SMILE** IN 7 DAYS

HELPS PREVENT CAVITIES

STRENGTHENS ENAMEL

FRESHENS BREATH

473mL

(16 FL OZ)